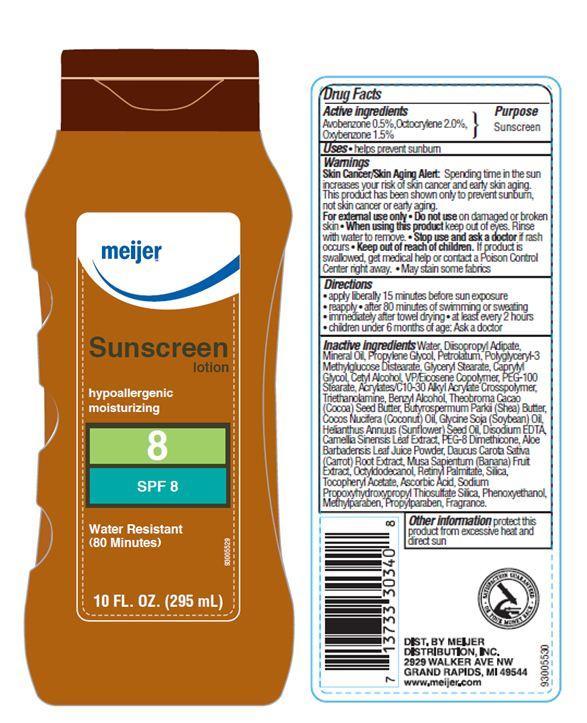 DRUG LABEL: Meijer SPF 8
NDC: 41250-001 | Form: LOTION
Manufacturer: Meijer Distribution Inc
Category: otc | Type: HUMAN OTC DRUG LABEL
Date: 20120802

ACTIVE INGREDIENTS: AVOBENZONE 0.5 mL/100 mL; OCTOCRYLENE 2 mL/100 mL; OXYBENZONE 1.5 mL/100 mL
INACTIVE INGREDIENTS: WATER; DIISOPROPYL ADIPATE; MINERAL OIL; PROPYLENE GLYCOL; PETROLATUM; CAPRYLYL GLYCOL; CETYL ALCOHOL; GLYCERYL MONOSTEARATE; PEG-100 STEARATE; CARBOMER INTERPOLYMER TYPE A (55000 CPS); TROLAMINE; BENZYL ALCOHOL; COCOA BUTTER; SHEA BUTTER; COCONUT OIL; SUNFLOWER OIL; EDETATE DISODIUM; GREEN TEA LEAF; PEG-8 DIMETHICONE; ALOE VERA LEAF; CARROT; BANANA; OCTYLDODECANOL; VITAMIN A PALMITATE; SILICON DIOXIDE; .ALPHA.-TOCOPHEROL ACETATE; ASCORBIC ACID; PHENOXYETHANOL; METHYLPARABEN; PROPYLPARABEN

Drug Facts

Active Ingredients

Avobenzone 0.5%
Octocrylene 2.0%
Oxybenzone 1.5%

Purpose

Sunscreen

Uses

- Helps prevent sunburn
- If used as directed with other sun protection measures (see Directions), decrease the risk of skin cancer and early skin aging caused by the sun.

Warnings

Skin Cancer/Skin Aging Alert: Spending time in the sun increases your risk of skin cancer and early skin aging. This product has been shown only to prevent sunburn, not skin cancer or early aging.

For external use only. Do not use on broken or damaged skin.

When using this product

Keep out of eyes. Rinse with water to remove.

Stop use and ask a doctor

if rash occurs

Keep out of reach of children

If swallowed, get medical help or contact a Poison Control Center right away. May stain some fabrics.

Directions

- apply liberally 15 minutes before sun exposure
- reapply
- after 80 minutes of swimming or sweating
- immediately after towel drying
- at least every 2 hours
- children under 6 months of age: Ask a doctor

Inactive ingredients

Water, Diisopropyl Adipate, Mineral Oil, Propylene Glycol, Petrolatum, Polyglyceryl-3 Methylglucose Distearate, Caprylyl Glycol, Cetyl Alcohol, Glyceryl Stearate, PEG-100 Stearate, VP/Eicosene Copolymer, Acrylates/C10-30 Alkyl Acrylate Crosspolymer, Triethanolamine, Benzyl Alcohol, Theobroma Cacao (Cocoa) Seed Butter, Butyrospermum Parkii (Shea) Butter, Cocos Nucifera (Coconut) Oil, Glycine Soja (Soybean) Oil, Helianthus Annuus (Sunflower) Seed Oil, Disodium EDTA, Camellia Sinensis Leaf Extract, PEG-8 Dimethicone, Aloe Barbadensis Leaf Juice Powder, Daucus Carota Sativa (Carrot) Root Extract, Musa Sapientum (Banana) Fruit Extract, Octyldodecanol, Retinyl Palmitate, Silica, Tocopheryl Acetate, Ascorbic Acid, Sodium Propoxyhydroxypropyl Thiosulfate Silica, Phenoxyethanol, Methylparaben, Propylparaben, Fragrance.

Other Information

protect this product from excessive heat and direct sun